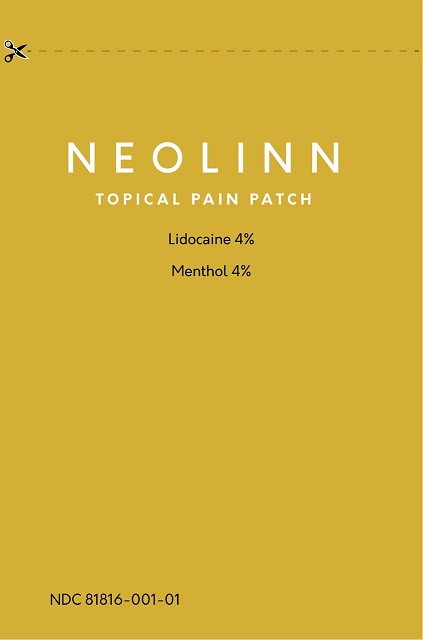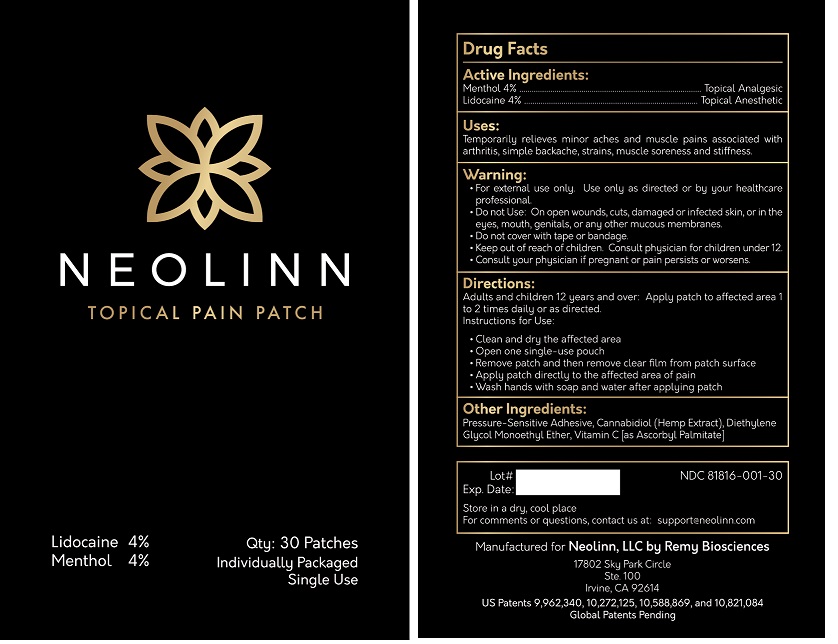 DRUG LABEL: NEOLINN
NDC: 81816-001 | Form: PATCH
Manufacturer: REMY Biosciences, Inc.
Category: otc | Type: HUMAN OTC DRUG LABEL
Date: 20210602

ACTIVE INGREDIENTS: LIDOCAINE 12 mg/300 mg; LEVOMENTHOL 12 mg/300 mg
INACTIVE INGREDIENTS: CANNABIDIOL; DIETHYLENE GLYCOL MONOETHYL ETHER; ASCORBYL PALMITATE; TRIMETHYLSILYL TREATED DIMETHICONOL/TRIMETHYLSILOXYSILICATE CROSSPOLYMER (45/55 W/W; 100000 PA.S); TRIMETHYLSILYL TREATED DIMETHICONOL/TRIMETHYLSILOXYSILICATE CROSSPOLYMER (40/60 W/W; 5000000 PA.S)

NEOLINN Topical Pain Patch

Drug Facts

Active Ingredients:

Menthol 4%

Lidocaine 4%

Purpose:

Menthol ....................Topical Analgesic

Lidocaine ..................Topical Anisthetic

Uses:

Temporarily relieves minor aches and muscle pains associated with

arthritis, simple backache, strains, muscle soreness and stiffness.

Warnings

• For external use only. Use only as directed by your healthcare

professional.

• Do not use: On open wounds, cuts, damaged or infevted skin, or in the

eyes, mouth, genitals, or or any other mucus membrane.

• Do not cover with tape or bandage.

• Keep out of reach of children. Consult physician for children under 12.

• Consult your physician if pregnant or pain persists or worsens.

Directions:

Adults and children 12 years and over: Apply patch to affected area 1

to 2 times daily or as directed.

Instructions for use:

• Clean and dry the affected area

• Open one single-use pouch

• Remove patch and then remove clear film from patch surface

• Apply patch directly to the affected area of pain

• Wash hands with soap and water ater applyinfg patch

INACTIVE INGREDIENT

Other Ingredients:

Presure Sensitive Adhesive, Cannabidiol (Hemp Extract), Diethylene

Glycol Monoethyl Ether, Vitamin C [as Ascorbyl Palmitate]

Package Labeling

NEOLINN

TOPICAL PAIN PATCH

Lidocaine 4% Qty: 30 Patches

Menthol 4% Individually Packaged

Single Use

Lot# NDC 81816-001-30

Exp. Date

Store in a dry, cool place.

For comments or questions, contact us at: support@neolinn.com

Manufactured for Neolinn, LLC by Remy Biosciences

17802 Sky Park Circle

Ste. 100

Irvine, CA 92614

Box

Pouch

res